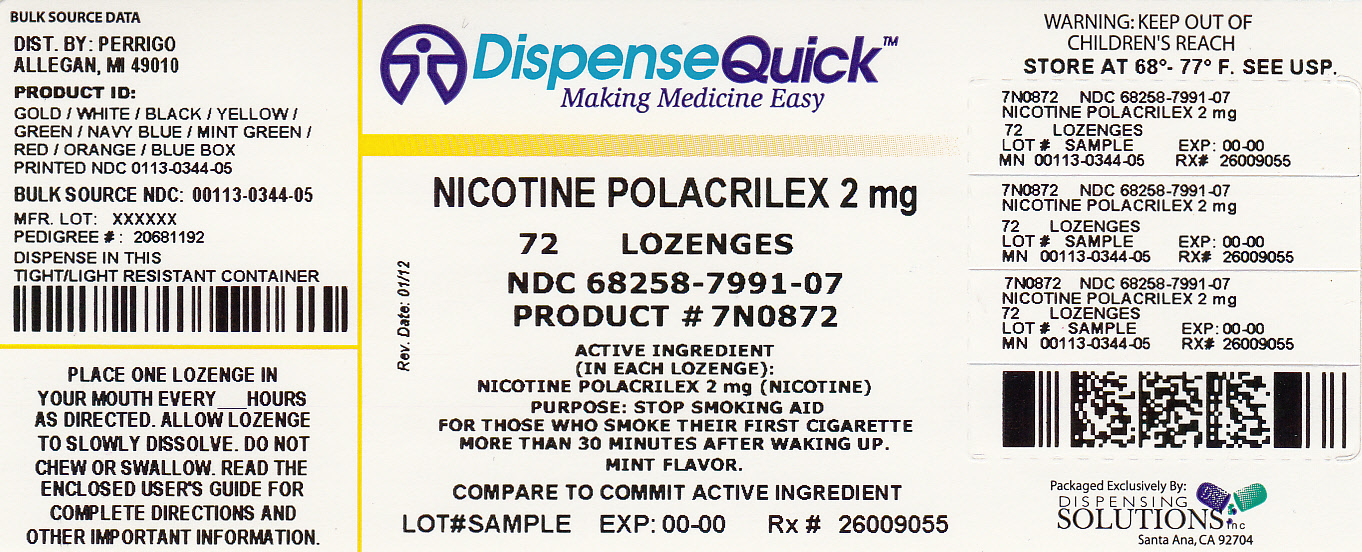 DRUG LABEL: Good Sense Nicotine
NDC: 68258-7991 | Form: LOZENGE
Manufacturer: Dispensing Solutions, Inc.
Category: otc | Type: HUMAN OTC DRUG LABEL
Date: 20120307

ACTIVE INGREDIENTS: NICOTINE 2 mg/1 1
INACTIVE INGREDIENTS: ASPARTAME; MAGNESIUM STEARATE; MANNITOL; POTASSIUM BICARBONATE; SODIUM ALGINATE; SODIUM CARBONATE; XANTHAN GUM

Perrigo Nicotine Lozenge Drug Facts

Active ingredient (in each lozenge)

Nicotine polacrilex, 2 mg (nicotine)

Purpose

Stop smoking aid

Uses

- reduces withdrawal symptoms, including nicotine craving associated with quitting smoking

Warnings

Enter section text here

If you are pregnant or breast-feeding,

only use this medicine on the advice of your health care provider. Smoking can seriously harm your child. Try to stop smoking without using any nicotine replacement medicine. This medicine is believed to be safer than smoking. However, the risks to your child from this medicine are not fully known.

Do not use

- if you continue to smoke, chew tobacco, use snuff, or use a nicotine patch or other nicotine containing products

Ask a doctor before use if you have

- a sodium-restricted diet
- heart disease, recent heart attack, or irregular heartbeat. Nicotine can increase your heart rate.
- high blood pressure not controlled with medication. Nicotine can increase your blood pressure.
- stomach ulcer or diabetes

Ask a doctor or pharmacist before use if you are

- using a non-nicotine stop smoking drug
- taking prescription medicine for depression or asthma. Your prescription dose may need to be adjusted.

Stop use and ask a doctor if

- mouth problems occur
- persistent indigestion or severe sore throat occurs
- irregular heartbeat or palpitations occur
- you get symptoms of nicotine overdose such as nausea, vomiting, dizziness, diarrhea, weakness or rapid heartbeat

Keep out of reach of children and pets.

Nicotine lozenges may have enough nicotine to make children and pets sick. If you need to remove the lozenge, wrap it in paper and throw away in the trash. In case of overdoe, get medical help or contact a Poison Control Center right away.

Directions

- if you are under 18 years of age, ask a doctor before use
- before using this product, read the enclosed User’s Guide for complete directions and other important information
- stop smoking completely when you begin using the lozenge
- if you smoke your first cigarette within 30 minutes of waking up, use 4 mg nicotine lozenge
- if you smoke your first cigarette more than 30 minutes after waking up, use 2 mg nicotine lozenge according to the following 12 week schedule:

Weeks 1 to 6 | Weeks 7 to 9 | Weeks 10 to 12
1 lozenge every; 1 to 2 hours | 1 lozenge every; 2 to 4 hours | 1 lozenge every; 4 to 8 hours

- nicotine lozenge is a medicine and must be used a certain way to get the best results
- place the lozenge in your mouth and allow the lozenge to slowly dissolve (about 20-30 minutes). Minimize swallowing. Do not chew or swallow lozenge.
- you may feel a warm or tingling sensation
- occasionally move the lozenge from one side of your mouth to the other until completely dissolved (about 20-30 minutes)
- do not eat or drink 15 minutes before using or while the lozenge is in your mouth
- to improve your chances of quitting, use at least 9 lozenges per day for the first 6 weeks
- do not use more than one lozenge at a time or continuously use one lozenge after another since this may cause you hiccups, heartburn, nausea or other side effects
- do not use more than 5 lozenges in 6 hours. Do not use more than 20 lozenges per day.
- stop using the nicotine lozenge at the end of 12 weeks. If you still feel the need to use nicotine lozenges, talk to your doctor.

Other information

- each lozenge contains: sodium 15 mg
- Phenylketonurics: Contains Phenylalanine 5.1 mg per lozenge
- sugar alcohol content: 1 g mannitol per lozenge
- store at 20-25°C (68-77°F)
- keep vial closed and protect from light

Inactive ingredients

aspartame, flavor, magnesium stearate, mannitol, potassium bicarbonate, sodium alginate, sodium carbonate, xanthan gum

Questions or comments?

call toll-free 1-866-751-9303

Principal Display Panel

NDC 68258-7991-07